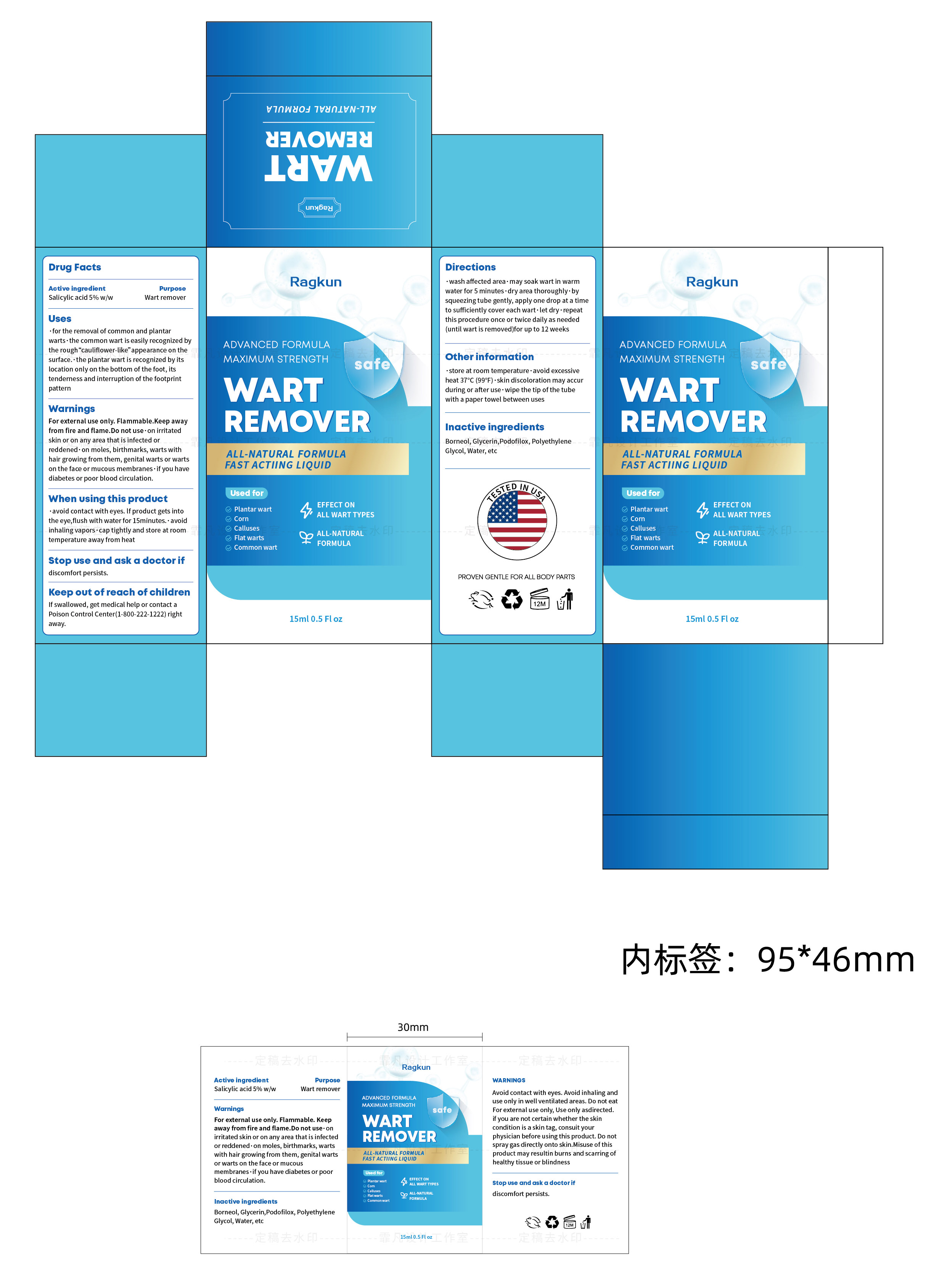 DRUG LABEL: Ragkun WART REMOVER
NDC: 84433-002 | Form: LIQUID
Manufacturer: Shenzhen Jiucai Ecommerce Co., Ltd
Category: otc | Type: HUMAN OTC DRUG LABEL
Date: 20240902

ACTIVE INGREDIENTS: SALICYLIC ACID 5 g/100 mL
INACTIVE INGREDIENTS: GLYCERIN; BORNEOL; POLYETHYLENE GLYCOL, UNSPECIFIED; PODOFILOX; WATER

Ragkun WART REMOVER

ACTIVE INGREDIENT

Salicylic acid 5%

PURPOSE

Wart remover

Keep out of reach of children
If swallowed, get medical help or contact aPoison Control Center(1-800-222-1222)rightaway.

INDICATIONS AND USAGE

.for the removal of common and plantarwarts·the common wart is easily recognized bythe rough“cauliflower-like”appearance on thesurface.·the plantar wart is recognized by itslocation only on the bottom of the foot, itstenderness and interruption of the footprintpattern

WARNINGS

For external use only. Flammable.Keep awayfrom fire and flame.Do not use·on irritatedskin or on any area that is infected orreddened·on moles, birthmarks, warts withhair growing from them, genital warts or wartson the face or mucous membranes ·if you havediabetes or poor blood circulation.

DOSAGE AND ADMINISTRATION

·wash affected area·may soak wart in warmwater for 5 minutes ·dry area thoroughly·bysqueezingtube gently, apply one drop at a timeto sufficiently cover each wart.let dry·repeatthis procedure once or twice daily as needed(until wart is removed)for up to 12 weeks

STORAGE AND HANDLING

store at room temperature·avoid excessiveheat 37°C (99°F)·skin discoloration may accurduring or after use· wipe the tip of the tubewith a paper towel between uses

INACTIVE INGREDIENT

Borneol
Glycerin
Podofilox
Polyethylene Glycol
Water